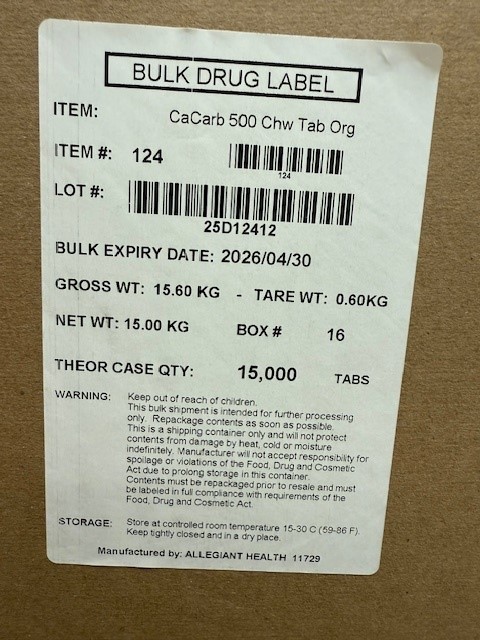 DRUG LABEL: Calcium Carbonate
NDC: 69168-124 | Form: TABLET, CHEWABLE
Manufacturer: Allegiant Health
Category: otc | Type: HUMAN OTC DRUG LABEL
Date: 20250501

ACTIVE INGREDIENTS: CALCIUM CARBONATE 500 mg/1 1
INACTIVE INGREDIENTS: FD&C YELLOW NO. 6 ALUMINUM LAKE; MAGNESIUM STEARATE; MALTODEXTRIN; SORBITOL

124 -Calcium Carbonate 500mg

Active ingredient(s)

Calcium carbonate USP 500mg

Purpose

Antacid

Use(s)

relieves

- heartburn
- sour stomach
- acid indigestion
- upset stomach associated with these symptoms

Warnings

Ask a doctor before use if you

- kidney disease
- taking any prescription drugs; antacids may interact with certain prescription drugs

When using this product

do not take more than 15 tablets in a 24 our period or use the maximum dosage of this product
for more than 2 weeks.

Directions

chew 2-4 tablets as symptoms occur, repeat hourly if needed

Other information

- Calcium content per tablets: 200mg
- store at 15°-30°C (59°-86°F)
- do not use if imprinted safety seal under cap is broken or
  missing

Inactive ingredients

FD&C yellow #6 aluminum lake, magnesium stearate, maltodextrin, orange flavor, sorbitol

Questions/Comments

Call 1-888-952-0050

(Monday-Friday 9 AM – 5 PM EST)

Principal Display Panel

Calcium Carbonate 500mg